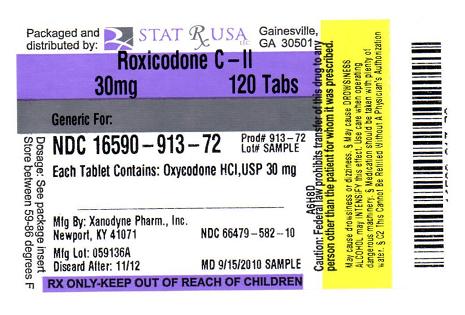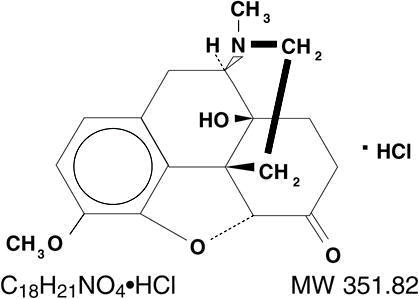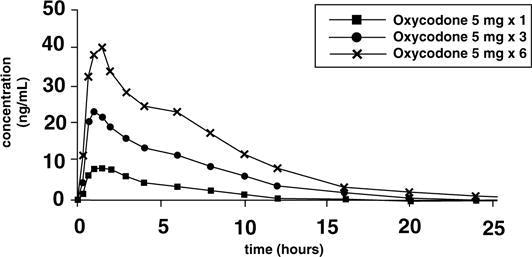 DRUG LABEL: Roxicodone
NDC: 16590-913 | Form: TABLET
Manufacturer: STAT RX USA LLC
Category: prescription | Type: HUMAN PRESCRIPTION DRUG LABEL
Date: 20101012
DEA Schedule: CII

ACTIVE INGREDIENTS: oxycodone hydrochloride 30 mg/1 1
INACTIVE INGREDIENTS: Cellulose, Microcrystalline; Stearic Acid; FD&C Blue No. 2; Sodium Starch Glycolate Type A Potato; Starch, Corn; Lactose Monohydrate; Water

ROXICODONE®
(Oxycodone Hydrochloride
Tablets USP)

CII
Rx only

DESCRIPTION

ROXICODONE® (oxycodone hydrochloride tablets USP) is an opioid analgesic.

Each tablet for oral administration contains 5 mg, 15 mg or 30 mg of oxycodone hydrochloride USP.

Oxycodone hydrochloride is a white, odorless crystalline powder derived from the opium alkaloid, thebaine. Oxycodone hydrochloride dissolves in water (1 g in 6 to 7 mL) and is considered slightly soluble in alcohol (octanol water partition coefficient is 0.7).

Chemically, oxycodone hydrochloride is 4, 5α-epoxy-14-hydroxy-3-methoxy-17-methylmorphinan-6-one hydrochloride and has the following structural formula:

The 5 mg ROXICODONE® tablet contains the following inactive ingredients: microcrystalline cellulose and stearic acid. The 15 and 30 mg tablets contain the following inactive ingredients: microcrystalline cellulose; sodium starch glycolate; corn starch; lactose; stearic acid; D&C Yellow No. 10 (15 mg tablet); and FD&C Blue No. 2 (15 mg and 30 mg tablets).

The 5 mg, 15 mg and 30 mg tablets contain the equivalent of 4.5 mg, 13.5 mg and 27.0 mg, respectively, of oxycodone free base.

CLINICAL PHARMACOLOGY

Pharmacology:

The analgesic ingredient, oxycodone, is a semi-synthetic narcotic with multiple actions qualitatively similar to those of morphine; the most prominent of these involves the central nervous system and organs composed of smooth muscle.

Oxycodone, as the hydrochloride salt, is a pure agonist opioid whose principal therapeutic action is analgesia and has been in clinical use since 1917. Like all pure opioid agonists, there is no ceiling effect to analgesia, such as is seen with partial agonists or non-opioid analgesics. Based upon a single-dose, relative-potency study conducted in humans with cancer pain, 10 to 15 mg of oxycodone given intramuscularly produced an analgesic effect similar to 10 mg of morphine given intramuscularly. Both drugs have a 3 to 4 hour duration of action. Oxycodone retains approximately one half of its analgesic activity when administered orally.

Effects on Central Nervous System: The precise mechanism of the analgesic action is unknown. However, specific CNS opioid receptors for endogenous compounds with opioid-like activity have been identified throughout the brain and spinal cord and play a role in the analgesic effects of this drug. A significant feature of opioid-induced analgesia is that it occurs without loss of consciousness. The relief of pain by morphine-like opioids is relatively selective, in that other sensory modalities, (e.g., touch, vibrations, vision, hearing, etc.) are not obtunded.

Oxycodone produces respiratory depression by direct action on brain stem respiratory centers. The respiratory depression involves both a reduction in the responsiveness of the brain stem respiratory centers to increases in carbon dioxide tension and to electrical stimulation.

Oxycodone depresses the cough reflex by direct effect on the cough center in the medulla. Antitussive effects may occur with doses lower than those usually required for analgesia. Oxycodone causes miosis, even in total darkness. Pinpoint pupils are a sign of opioid overdose but are not pathognomonic (e.g., pontine lesions of hemorrhagic or ischemic origins may produce similar findings). Marked mydriasis rather than miosis may be seen due to hypoxia in overdose situations.

Effects on Gastrointestinal Tract And Other Smooth Muscle: Oxycodone, like other opioid analgesics, produces some degree of nausea and vomiting which is caused by direct stimulation of the chemoreceptor trigger zone (CTZ) located in the medulla. The frequency and severity of emesis gradually diminishes with time.

Oxycodone may cause a decrease in the secretion of hydrochloric acid in the stomach that reduces motility while increasing the tone of the antrum, stomach, and duodenum. Digestion of food in the small intestine is delayed and propulsive contractions are decreased. Propulsive peristaltic waves in the colon are decreased, while tone may be increased to the point of spasm resulting in constipation. Other opioid-induced effects may include a reduction in biliary and pancreatic secretions, spasm of sphincter of Oddi, and transient elevations in serum amylase.

Effects on Cardiovascular System: Oxycodone, in therapeutic doses, produces peripheral vasodilatation (arteriolar and venous), decreased peripheral resistance, and inhibits baroreceptor reflexes. Manifestations of histamine release and/or peripheral vasodilatation may include pruritus, flushing, red eyes, sweating, and/or orthostatic hypotension.

Caution should be used in hypovolemic patients, such as those suffering acute myocardial infarction, because oxycodone may cause or further aggravate their hypotension. Caution should also be used in patients with cor pulmonale who have received therapeutic doses of opioids.

Pharmacodynamics:

The relationship between the plasma level of oxycodone and the analgesic response will depend on the patient's age, state of health, medical condition and extent of previous opioid treatment.

The minimum effective plasma concentration of oxycodone to achieve analgesia will vary widely among patients, especially among patients who have been previously treated with potent agonist opioids. Thus, patients need to be treated with individualized titration of dosage to the desired effect. The minimum effective analgesic concentration of oxycodone for any individual patient may increase with repeated dosing due to an increase in pain and/or development of tolerance.

Pharmacokinetics:

The activity of ROXICODONE® (oxycodone hydrochloride) tablets is primarily due to the parent drug oxycodone. ROXICODONE® tablets are designed to provide immediate release of oxycodone.

Table 1 Pharmacokinetic Parameters (Mean±SD)
Dose\Parameters | AUC | Cmax | Tmax | Cmin | Cavg | Half-Life
 | (ngxhr/mL) | (ng/mL) | (hr) | (ng/mL) | (ng/mL) | (hr)
Single Dose
Pharmacokinetics
ROXICODONE | 133.2±33 | 22.3±8.2 | 1.8±1.8 | n/a | n/a | 3.73±0.9
5 mg tabs x 3
ROXICODONE | 128.2±35.1 | 22.2±7.6 | 1.4±0.7 | n/a | n/a | 3.55±1.0
15 mg tab
ROXICODONE Liquid | 130.6±34.7 | 21.1±6.1 | 1.9±1.5 | n/a | n/a | 3.71±0.8
Concentrate
15 mg oral solution
ROXICODONE | 268.2±60.7 | 39.3±14.0 | 2.6±3.0 | n/a | n/a | 3.85±1.3
30 mg tab
Food-Effect,
Single Dose
ROXICODONE | 105±6.2 | 19.0±3.7 | 1.25±0.5 | n/a | n/a | 2.9±0.4
10 mg/10 mL
oral sol'n (fasted)
ROXICODONE | 133±25.2 | 17.7±3.0 | 2.54±1.2 | n/a | n/a | 3.3±0.5
10 mg/10 mL
oral sol'n (fed)
Multiple-Dose | AUC(72-84)
Studies
ROXICODONE | 113.3±24.0 | 15.7±3.2 | 1.3±0.3 | 7.4±1.8 | 9.4±2.0 | n/a
5 mg tabs
q6h x 14 doses
ROXICODONE | 99.0±24.8 | 12.9±3.1 | 1.0±0.3 | 7.2±2.3 | 9.7±2.6 | n/a
3.33 mg (3.33 mL)
oral sol'n. q4h x 21
doses

Absorption: About 60% to 87% of an oral dose of oxycodone reaches the systemic circulation in comparison to a parenteral dose. This high oral bioavailability (compared to other oral opioids) is due to lower pre-systemic and/or first-pass metabolism of oxycodone. The relative oral bioavailability of ROXICODONE® 15 mg and 30 mg tablets, compared to the 5 mg ROXICODONE® tablets, is 96% and 101% respectively. ROXICODONE® 15 mg tablets and 30 mg tablets are bioequivalent to the 5 mg ROXICODONE® tablet (see Table 1 for pharmacokinetic parameters). Dose proportionality of oxycodone has been established using the ROXICODONE® 5 mg tablets at doses of 5 mg, 15 mg (three 5 mg tablets) and 30 mg (six 5 mg tablets) based on extent of absorption (AUC) (see Figure 1). It takes approximately 18 to 24 hours to reach steady-state plasma concentrations of oxycodone with ROXICODONE®.

Figure 1 - Roxicodone Dose-Proportionality Study 5 mg, 15 mg and 30 mg (single-dose)

Food Effect: A single-dose food effect study was conducted in normal volunteers using the 5 mg/5 mL solution. The concurrent intake of a high fat meal was shown to enhance the extent (27% increase in AUC), but not the rate of oxycodone absorption from the oral solution (see Table 1). In addition, food caused a delay in Tmax (1.25 to 2.54 hour). Similar effects of food are expected with the 15 mg and 30 mg tablets.

Distribution: Following intravenous administration, the volume of distribution (Vss) for oxycodone was 2.6 L/kg. Plasma protein binding of oxycodone at 37°C and a pH of 7.4 was about 45%. Oxycodone has been found in breast milk (see PRECAUTIONS-Nursing Mothers).

Metabolism: Oxycodone hydrochloride is extensively metabolized to noroxycodone, oxymorphone, and their glucuronides. The major circulating metabolite is noroxycodone with an AUC ratio of 0.6 relative to that of oxycodone. Oxymorphone is present in the plasma only in low concentrations. The analgesic activity profile of other metabolites is not known at present.

The formation of oxymorphone, but not noroxycodone, is mediated by CYP2D6 and as such its formation can, in theory, be affected by other drugs (see PRECAUTIONS-Drug Interactions).

Elimination: Oxycodone and its metabolites are excreted primarily via the kidney. The amounts measured in the urine have been reported as follows: free oxycodone up to 19%; conjugated oxycodone up to 50%; free oxymorphone 0%; conjugated oxymorphone ≤ 14%; both free and conjugated noroxycodone have been found in the urine but not quantified. The total plasma clearance was 0.8 L/min for adults. Apparent elimination half-life of oxycodone following the administration of ROXICODONE® was 3.5 to 4 hours.

Special Populations:

Geriatric: Population pharmacokinetic studies conducted with ROXICODONE®, indicated that the plasma concentrations of oxycodone did not appear to be increased in patients over the age of 65.

Gender: Population pharmacokinetic analyses performed in the clinical study support the lack of gender effect on the pharmacokinetics of oxycodone from ROXICODONE®.

Race: Population pharmacokinetic analyses support the lack of race effect on oxycodone pharmacokinetics after administration of ROXICODONE®, but these data should be interpreted conservatively, since the majority of patients enrolled into the studies were Caucasians (94%).

Renal Insufficiency: In a clinical trial supporting the development of ROXICODONE®, too few patients with decreased renal function were evaluated to study these potential differences. In previous studies, patients with renal impairment (defined as a creatinine clearance < 60 mL/min) had concentrations of oxycodone in the plasma that were higher than in subjects with normal renal function. Based on information available on the metabolism and excretion of oxycodone, dose initiation in patients with renal impairment should follow a conservative approach. Dosages should be adjusted according to the clinical situation.

Hepatic Failure: In a clinical trial supporting the development of ROXICODONE®, too few patients with decreased hepatic function were evaluated to study these potential differences. However, since oxycodone is extensively metabolized, its clearance may decrease in hepatic failure patients. Dose initiation in patients with hepatic impairment should follow a conservative approach. Dosages should be adjusted according to the clinical situation.

INDICATIONS AND USAGE

ROXICODONE® tablets are an immediate-release oral formulation of oxycodone hydrochloride indicated for the management of moderate to severe pain where the use of an opioid analgesic is appropriate.

CONTRAINDICATIONS

ROXICODONE® is contraindicated in patients with known hypersensitivity to oxycodone, or in any situation where opioids are contraindicated. This includes patients with significant respiratory depression (in unmonitored settings or the absence of resuscitative equipment) and patients with acute or severe bronchial asthma or hypercarbia. ROXICODONE® is contraindicated in any patient who has or is suspected of having paralytic ileus.

WARNINGS

Respiratory Depression:

Respiratory depression is the chief hazard from all opioid agonist preparations. Respiratory depression occurs most frequently in elderly or debilitated patients, usually following large initial doses in non-tolerant patients, or when opioids are given in conjunction with other agents that depress respiration.

ROXICODONE® should be used with extreme caution in patients with significant chronic obstructive pulmonary disease or cor pulmonale, and in patients having substantially decreased respiratory reserve, hypoxia, hypercapnia, or pre-existing respiratory depression. In such patients, even usual therapeutic doses of ROXICODONE® may decrease respiratory drive to the point of apnea. In these patients alternative non-opioid analgesics should be considered, and opioids should be employed only under careful medical supervision at the lowest effective dose.

Hypotensive Effect:

ROXICODONE®, like all opioid analgesics, may cause severe hypotension in an individual whose ability to maintain blood pressure has been compromised by a depleted blood volume, or after concurrent administration with drugs such as phenothiazines or other agents which compromise vasomotor tone. ROXICODONE® may produce orthostatic hypotension in ambulatory patients. ROXICODONE®, like all opioid analgesics, should be administered with caution to patients in circulatory shock, since vasodilatation produced by the drug may further reduce cardiac output and blood pressure.

Head Injury and Increased Intracranial Pressure:

The respiratory depressant effects of narcotics and their capacity to elevate cerebrospinal fluid pressure may be markedly exaggerated in the presence of head injury, other intracranial lesions or a pre-existing increase in intracranial pressure. Furthermore, narcotics produce adverse reactions which may obscure the clinical course of patients with head injuries.

PRECAUTIONS

General:

ROXICODONE® tablets are intended for use in patients who require oral pain therapy with an opioid agonist. As with any opioid analgesic, it is critical to adjust the dosing regimen individually for each patient (see DOSAGE AND ADMINISTRATION).

Selection of patients for treatment with ROXICODONE® should be governed by the same principles that apply to the use of other potent opioid analgesics. Opioid analgesics given on a fixed-dosage schedule have a narrow therapeutic index in certain patient populations, especially when combined with other drugs, and should be reserved for cases where the benefits of opioid analgesia outweigh the known risks of respiratory depression, altered mental state, and postural hypotension. Physicians should individualize treatment in every case, using nonopioid analgesics, prn opioids and /or combination products, and chronic opioid therapy with drugs such as ROXICODONE® (oxycodone hydrochloride) in a progressive plan of pain management such as outlined by the World Health Organization, the Agency for Health Care Policy and Research, and the American Pain Society.

Use of ROXICODONE® is associated with increased potential risks and should be used only with caution in the following conditions: acute alcoholism; adrenocortical insufficiency (e.g., Addison's disease); convulsive disorders; CNS depression or coma; delirium tremens; debilitated patients; kyphoscoliosis associated with respiratory depression; myxedema or hypothyroidism; prostatic hypertrophy or urethral stricture; severe impairment of hepatic, pulmonary or renal function; and toxic psychosis.

The administration of ROXICODONE®, like all opioid analgesics, may obscure the diagnosis or clinical course in patients with acute abdominal conditions. Oxycodone may aggravate convulsions in patients with convulsive disorders, and all opioids may induce or aggravate seizures in some clinical settings.

Tolerance and Physical Dependence:

Physical dependence and tolerance are not unusual during chronic opioid therapy. Significant tolerance should not occur in most patients treated with the lowest doses of oxycodone. It should be expected, however, that a fraction of patients will develop some degree of tolerance and require progressively higher dosages of ROXICODONE® to maintain pain control during chronic treatment. The dosage should be selected according to the patient's individual analgesic response and ability to tolerate side effects. Tolerance to the analgesic effects of opioids is usually paralleled by tolerance to side effects except for constipation.

Physical dependence results in withdrawal symptoms in patients who abruptly discontinue the drug or may be precipitated through the administration of drugs with opioid antagonist activity. If ROXICODONE® is abruptly discontinued in a physically dependent patient, an abstinence syndrome may occur (see DRUG ABUSE AND DEPENDENCE). If signs and symptoms of withdrawal occur, patients should be treated by reinstitution of opioid therapy followed by gradual tapered dose reduction of ROXICODONE® combined with symptomatic support (see DOSAGE AND ADMINISTRATION: Cessation of Therapy).

Use In Pancreatic/Biliary Tract Disease:

ROXICODONE® may cause spasm of the sphincter of Oddi and should be used with caution in patients with biliary tract disease, including acute pancreatitis. Opioids like ROXICODONE® may cause increases in the serum amylase level.

Information for Patients/Caregivers:

If clinically advisable, patients (or their caregivers) receiving ROXICODONE® (oxycodone hydrochloride) tablets should be given the following information by the physician, nurse, pharmacist or caregiver:

1. Patients should be advised to report episodes of breakthrough pain and adverse experiences occurring during therapy. Individualization of dosage is essential to make optimal use of this medication.
2. Patients should be advised not to adjust the dose of ROXICODONE® without consulting the prescribing professional.
3. Patients should be advised that ROXICODONE® may impair mental and/or physical ability required for the performance of potentially hazardous tasks (e.g., driving, operating heavy machinery).
4. Patients should not combine ROXICODONE® with alcohol or other central nervous system depressants (sleep aids, tranquilizers) except by the orders of the prescribing physician, because additive effects may occur.
5. Women of childbearing potential who become, or are planning to become pregnant, should be advised to consult their physician regarding the effects of analgesics and other drug use during pregnancy on themselves and their unborn child.
6. Patients should be advised that ROXICODONE® is a potential drug of abuse. They should protect it from theft, and it should never be given to anyone other than the individual for whom it was prescribed.
7. Patients should be advised that if they have been receiving treatment with ROXICODONE® for more than a few weeks and cessation of therapy is indicated, it may be appropriate to taper the ROXICODONE® dose, rather than abruptly discontinue it, due to the risk of precipitating withdrawal symptoms. Their physician can provide a dose schedule to accomplish a gradual discontinuation of the medication.

Drug Interactions:

Oxycodone is metabolized in part to oxymorphone via the cytochrome p450 isoenzyme CYP2D6. While this pathway may be blocked by a variety of drugs (e.g., certain cardiovascular drugs and antidepressants), such blockade has not yet been shown to be of clinical significance with this agent. However, clinicians should be aware of this possible interaction.

Neuromuscular Blocking Agents: Oxycodone, as well as other opioid analgesics, may enhance the neuromuscular blocking action of skeletal muscle relaxants and produce an increased degree of respiratory depression.

CNS Depressants: Patients receiving narcotic analgesics, general anesthetics, phenothiazines, other tranquilizers, sedative-hypnotics or other CNS depressants (including alcohol) concomitantly with ROXICODONE® may exhibit an additive CNS depression. Interactive effects resulting in respiratory depression, hypotension, profound sedation, or coma may result if these drugs are taken in combination with the usual dosage of ROXICODONE®. When such combined therapy is contemplated, the dose of one or both agents should be reduced.

Mixed Agonist/Antagonist Opioid Analgesics: Agonist/antagonist analgesics (i.e., pentazocine, nalbuphine, butorphanol and buprenorphine) should be administered with caution to patients who have received or are receiving a course of therapy with a pure opioid agonist analgesic such as ROXICODONE®. In this situation, mixed agonist/antagonist analgesics may reduce the analgesic effect of ROXICODONE® and/or may precipitate withdrawal symptoms in these patients.

Monoamine Oxidase Inhibitors (MAOIs): MAOIs have been reported to intensify the effects of at least one opioid drug causing anxiety, confusion and significant depression of respiration or coma. The use of ROXICODONE® is not recommended for patients taking MAOIs or within 14 days of stopping such treatment.

Carcinogenesis, Mutagenesis, Impairment of Fertility:

Long-term studies have not been performed in animals to evaluate the carcinogenic potential of ROXICODONE® or oxycodone. The possible effects on male or female fertility have not been studied in animals.

Oxycodone hydrochloride was genotoxic in an in vitro mouse lymphoma assay in the presence of metabolic activation. There was no evidence of genotoxic potential in an in vitro bacterial reverse mutation assay (Salmonella typhimurium and Escherichia coli) or in an assay for chromosomal aberrations (in vivo mouse bone marrow micronucleus assay).

Pregnancy:

TERATOGENIC EFFECTS

Teratogenic Effects: Category B: Reproduction studies in Sprague-Dawley rats and New Zealand rabbits revealed that when oxycodone was administered orally at doses up to 16 mg/kg (approximately 2 times the daily oral dose of 90 mg for adults on a mg/m^2 basis) and 25 mg/kg (approximately 5 times the daily oral dose of 90 mg on a mg/m^2 basis), respectively was not teratogenic or embryo-fetal toxic. There are no adequate and well controlled studies of oxycodone in pregnant women. Because animal reproductive studies are not always predictive of human responses, ROXICODONE® should be used during pregnancy only if potential benefit justifies the potential risk to the fetus.

NONTERATOGENIC EFFECTS

Nonteratogenic Effects: Neonates whose mothers have taken oxycodone chronically may exhibit respiratory depression and/or withdrawal symptoms, either at birth and/or in the nursery.

Labor and Delivery:

ROXICODONE® is not recommended for use in women during or immediately prior to labor. Occasionally, opioid analgesics may prolong labor through actions which temporarily reduce the strength, duration and frequency of uterine contractions. Neonates, whose mothers received opioid analgesics during labor, should be observed closely for signs of respiratory depression. A specific narcotic antagonist, naloxone, should be available for reversal of narcotic-induced respiratory depression in the neonate.

Nursing Mothers:

Oxycodone has been detected in breast milk. Withdrawal symptoms can occur in breast-feeding infants when maternal administration of an opioid analgesic is stopped. Ordinarily, nursing should not be undertaken while a patient is receiving ROXICODONE® since oxycodone may be excreted in milk.

Pediatric Use:

The safety and efficacy of oxycodone in pediatric patients have not been evaluated.

Geriatric Use:

Of the total number of subjects in clinical studies of ROXICODONE®, 20.8% (112/538) were 65 and over, while 7.2% (39/538) were 75 and over. No overall differences in safety or effectiveness were observed between these subjects and younger subjects, and other reported clinical experience has not identified differences in responses between the elderly and younger patients, but greater sensitivity of some older individuals cannot be ruled out.

Hepatic Impairment:

Since oxycodone is extensively metabolized, its clearance may decrease in hepatic failure patients. Dose initiation in patients with hepatic impairment should follow a conservative approach. Dosages should be adjusted according to the clinical situation.

Renal Impairment:

Published data reported that elimination of oxycodone was impaired in end-stage renal failure. Mean elimination half-life was prolonged in uremic patients due to increased volume of distribution and reduced clearance. Dose initiation should follow a conservative approach. Dosages should be adjusted according to the clinical situation.

Ambulatory Patients:

ROXICODONE® may impair the mental and/or physical abilities required for the performance of potentially hazardous tasks such as driving a car or operating machinery. The patient using this drug should be cautioned accordingly.

ADVERSE REACTIONS

ROXICODONE® tablets have been evaluated in open label clinical trials in patients with cancer and nonmalignant pain. ROXICODONE® tablets are associated with adverse experiences similar to those seen with other opioids.

Serious adverse reactions that may be associated with ROXICODONE® therapy in clinical use are those observed with other opioid analgesics and include: respiratory depression, respiratory arrest, circulatory depression, cardiac arrest, hypotension, and/or shock (see OVERDOSE, WARNINGS).

The less severe adverse events seen on initiation of therapy with ROXICODONE® are also typical opioid side effects. These events are dose dependent, and their frequency depends on the clinical setting, the patient's level of opioid tolerance, and host factors specific to the individual. They should be expected and managed as a part of opioid analgesia. The most frequent of these include nausea, constipation, vomiting, headache, and pruritus.

In many cases the frequency of adverse events during initiation of opioid therapy may be minimized by careful individualization of starting dosage, slow titration and the avoidance of large rapid swings in plasma concentration of the opioid. Many of these adverse events will abate as therapy is continued and some degree of tolerance is developed, but others may be expected to remain throughout therapy.

In all patients for whom dosing information was available (n=191) from the open-label and double-blind studies involving ROXICODONE®, the following adverse events were recorded in ROXICODONE® treated patients with an incidence ≥ 3%. In descending order of frequency they were: nausea, constipation, vomiting, headache, pruritus, insomnia, dizziness, asthenia, and somnolence.

The following adverse experiences occurred in less than 3% of patients involved in clinical trials with oxycodone:

Body as a Whole: abdominal pain, accidental injury, allergic reaction, back pain, chills and fever, fever, flu syndrome, infection, neck pain, pain, photosensitivity reaction, and sepsis.

Cardiovascular: deep thrombophlebitis, heart failure, hemorrhage, hypotension, migraine, palpitation, and tachycardia.

Digestive: anorexia, diarrhea, dyspepsia, dysphagia, gingivitis, glossitis, and nausea and vomiting.

Hemic and Lymphatic: anemia and leukopenia.

Metabolic and Nutritional: edema, gout, hyperglycemia, iron deficiency anemia and peripheral edema.

Musculoskeletal: arthralgia, arthritis, bone pain, myalgia and pathological fracture.

Nervous: agitation, anxiety, confusion, dry mouth, hypertonia, hypesthesia, nervousness, neuralgia, personality disorder, tremor, and vasodilation.

Respiratory: bronchitis, cough increased, dyspnea, epistaxis, laryngismus, lung disorder, pharyngitis, rhinitis, and sinusitis.

Skin and Appendages: herpes simplex, rash, sweating, and urticaria.

Special Senses: amblyopia.

Urogenital: urinary tract infection.

DRUG ABUSE AND DEPENDENCE

Controlled Substance:

ROXICODONE® contains oxycodone, a mu-agonist opioid of the morphine type and is a Schedule II controlled substance. ROXICODONE®, like other opioids used in analgesia, can be abused and is subject to criminal diversion.

Abuse:

Drug addiction is characterized by compulsive use, use for non-medical purposes, and continued use despite harm or risk of harm. Drug addiction is a treatable disease, utilizing a multi-disciplinary approach, but relapse is common.

“Drug-seeking” behavior is very common in addicts and drug abusers. Drug-seeking tactics include emergency calls or visits near the end of office hours, refusal to undergo appropriate examination, testing or referral, repeated “loss” of prescriptions, tampering with prescriptions and reluctance to provide prior medical records or contact information for other treating physician(s). “Doctor shopping” to obtain additional prescriptions is common among drug abusers and people suffering from untreated addiction.

Abuse and addiction are separate and distinct from physical dependence and tolerance. Physicians should be aware that addiction may not be accompanied by concurrent tolerance and symptoms of physical dependence. In addition, abuse of opioids can occur in the absence of true addiction and is characterized by misuse for nonmedical purposes, often in combination with other psychoactive substances. Careful record-keeping of prescribing information, including quantity, frequency, and renewal requests is strongly advised.

ROXICODONE® is intended for oral use only. Abuse of ROXICODONE® poses a risk of overdose and death. The risk is increased with concurrent abuse of alcohol and other substances. Parenteral drug abuse is commonly associated with transmission of infectious diseases such as hepatitis and HIV.

Proper assessment of the patient, proper prescribing practices, periodic re-evaluation of therapy, and proper dispensing and storage are appropriate measures that help to limit abuse of opioid drugs.

Infants born to mothers physically dependent on opioids will also be physically dependent and may exhibit respiratory difficulties and withdrawal symptoms.

Dependence:

Tolerance is the need for increasing doses of opioids to maintain a defined effect such as analgesia (in the absence of disease progression or other external factors). Physical dependence is manifested by withdrawal symptoms after abrupt discontinuation of a drug or upon administration of an antagonist. Physical dependence and tolerance are not unusual during chronic opioid therapy.

The opioid abstinence or withdrawal syndrome is characterized by some or all of the following: restlessness, lacrimation, rhinorrhea, yawning, perspiration, chills, myalgia, and mydriasis. Other symptoms also may develop, including irritability, anxiety, backache, joint pain, weakness, abdominal cramps, insomnia, nausea, anorexia, vomiting, diarrhea, or increased blood pressure, respiratory rate, or heart rate. In general, opioids should not be abruptly discontinued.

OVERDOSAGE

Signs and Symptoms:

Acute overdose with ROXICODONE® can be manifested by respiratory depression, somnolence progressing to stupor or coma, skeletal muscle flaccidity, cold and clammy skin, constricted pupils, bradycardia, hypotension, and death.

Treatment:

To treat ROXICODONE® overdose, primary attention should be given to the re-establishment of a patent airway and institution of assisted or controlled ventilation. Supportive measures (including oxygen and vasopressors) should be employed in the management of circulatory shock and pulmonary edema accompanying overdose as indicated. Cardiac arrest or arrhythmias may require cardiac massage or defibrillation.

The narcotic antagonists, naloxone or nalmefene, are specific antidotes for opioid overdose. Opioid antagonists should not be administered in the absence of clinically significant respiratory or circulatory depression secondary to ROXICODONE® overdose. If needed the appropriate dose of naloxone hydrochloride or nalmefene should be administered simultaneously with efforts at respiratory resuscitation (see package insert for each drug for the details). Since the duration of action of oxycodone may exceed that of the antagonist, the patient should be kept under continued surveillance and repeated doses of the antagonist should be administered as needed to maintain adequate respiration. Gastric emptying may be useful in removing unabsorbed drug.

Opioid antagonists should be administered cautiously to persons who are suspected to be physically dependent on any opioid agonist, including oxycodone (see Opioid-Tolerant Individuals).

Opioid-Tolerant Individuals: In an individual physically dependent on opioids, administration of a usual dose of antagonist will precipitate an acute withdrawal. The severity of the withdrawal syndrome produced will depend on the degree of physical dependence and the dose of the antagonist administered. Use of an opioid antagonist should be reserved for cases where such treatment is clearly needed. If it is necessary to treat serious respiratory depression in the physically dependent patient, administration of the antagonist should be begun with care and by titration with smaller than usual doses.

DOSAGE AND ADMINISTRATION

ROXICODONE® is intended for the management of moderate to severe pain in patients who require treatment with an oral opioid analgesic. The dose should be individually adjusted according to severity of pain, patient response and patient size. If the pain increases in severity, if analgesia is not adequate, or if tolerance occurs, a gradual increase in dosage may be required.

Patients who have not been receiving opioid analgesics should be started on ROXICODONE® in a dosing range of 5 to 15 mg every 4 to 6 hours as needed for pain. The dose should be titrated based upon the individual patient's response to their initial dose of ROXICODONE®. Patients with chronic pain should have their dosage given on an around-the-clock basis to prevent the reoccurrence of pain rather than treating the pain after it has occurred. This dose can then be adjusted to an acceptable level of analgesia taking into account side effects experienced by the patient.

For control of severe chronic pain, ROXICODONE® should be administered on a regularly scheduled basis, every 4-6 hours, at the lowest dosage level that will achieve adequate analgesia.

As with any potent opioid, it is critical to adjust the dosing regimen for each patient individually, taking into account the patient's prior analgesic treatment experience. Although it is not possible to list every condition that is important to the selection of the initial dose of ROXICODONE®, attention should be given to: 1) the daily dose, potency, and characteristics of a pure agonist or mixed agonist/antagonist the patient has been taking previously, 2) the reliability of the relative potency estimate to calculate the dose of oxycodone needed, 3) the degree of opioid tolerance, 4) the general condition and medical status of the patient, and 5) the balance between pain control and adverse experiences.

Conversion From Fixed-Ratio Opioid/Acetaminophen, Opioid/Aspirin, or Opioid/Nonsteroidal Combination Drugs:

When converting patients from fixed ratio opioid/non-opioid drug regimens a decision should be made whether or not to continue the non-opioid analgesic. If a decision is made to discontinue the use of non-opioid analgesic, it may be necessary to titrate the dose of ROXICODONE® in response to the level of analgesia and adverse effects afforded by the dosing regimen. If the non-opioid regimen is continued as a separate single entity agent, the starting dose ROXICODONE® should be based upon the most recent dose of opioid as a baseline for further titration of oxycodone. Incremental increases should be gauged according to side effects to an acceptable level of analgesia.

Patients Currently on Opioid Therapy:

If a patient has been receiving opioid-containing medications prior to taking ROXICODONE®, the potency of the prior opioid relative to oxycodone should be factored into the selection of the total daily dose (TDD) of oxycodone.

In converting patients from other opioids to ROXICODONE® close observation and adjustment of dosage based upon the patient's response to ROXICODONE® is imperative. Administration of supplemental analgesia for breakthrough or incident pain and titration of the total daily dose of ROXICODONE® may be necessary, especially in patients who have disease states that are changing rapidly.

Maintenance of Therapy:

Continual re-evaluation of the patient receiving ROXICODONE® is important, with special attention to the maintenance of pain control and the relative incidence of side effects associated with therapy. If the level of pain increases, effort should be made to identify the source of increased pain, while adjusting the dose as described above to decrease the level of pain.

During chronic therapy, especially for non-cancer-related pain (or pain associated with other terminal illnesses), the continued need for the use of opioid analgesics should be re-assessed as appropriate.

Cessation of Therapy:

When a patient no longer requires therapy with ROXICODONE® or other opioid analgesics for the treatment of their pain, it is important that therapy be gradually discontinued over time to prevent the development of an opioid abstinence syndrome (narcotic withdrawal). In general, therapy can be decreased by 25% to 50% per day with careful monitoring for signs and symptoms of withdrawal (see DRUG ABUSE AND DEPENDENCE section for description of the signs and symptoms of withdrawal). If the patient develops these signs or symptoms, the dose should be raised to the previous level and titrated down more slowly, either by increasing the interval between decreases, decreasing the amount of change in dose, or both. It is not known at what dose of ROXICODONE® that treatment may be discontinued without risk of the opioid abstinence syndrome.

HOW SUPPLIED

ROXICODONE® (oxycodone hydrochloride tablets USP) are available as follows:

5 mg white scored tablets (Identified 54 582)
[Embossed 54 582 on one side]
NDC 66479-580-25: Unit dose, 25 tablets per card,
4 cards per shipper

NDC 66479-580-10: Bottles of 100 tablets

15 mg green tablets scored (Identified 54 710)
[Embossed 54 710 on one side]
NDC 66479-581-10: Bottles of 100 tablets

30 mg blue tablets scored (Identified 54 199)
[Embossed 54 199 on one side]
NDC 66479-582-10: Bottles of 100 tablets

DEA Order Form Required
Dispense in a tight, light-resistant container.
Protect from moisture.
Store at 25°C (77°F); excursions are permitted to
15°-30°C (59°-86°F) [see USP Controlled Room Temperature]

ROXICODONE® is a registered trademark of Xanodyne Pharmaceuticals, Inc.

© 2009 Xanodyne Pharmaceuticals, Inc.

Marketed by:

Xanodyne®
Pharmaceuticals, Inc.
Newport, KY 41071

PI - 580/581/582-A
Rev. 05-2009

To request medical information or to report suspected adverse reactions, contact Xanodyne Medical Affairs at 1-877-773-7793.

ROXICODONE LABEL